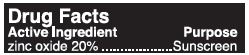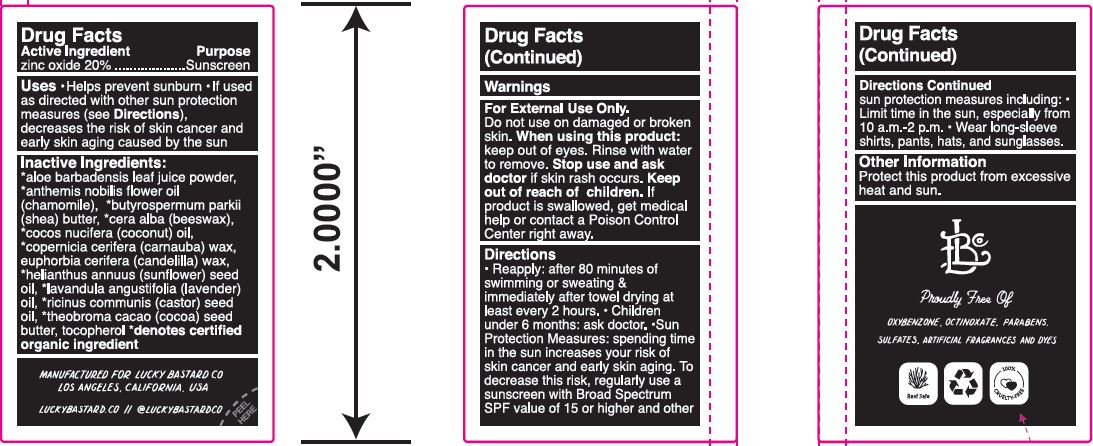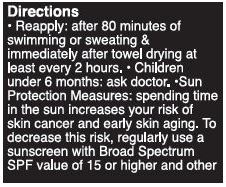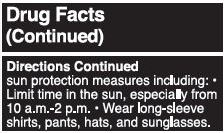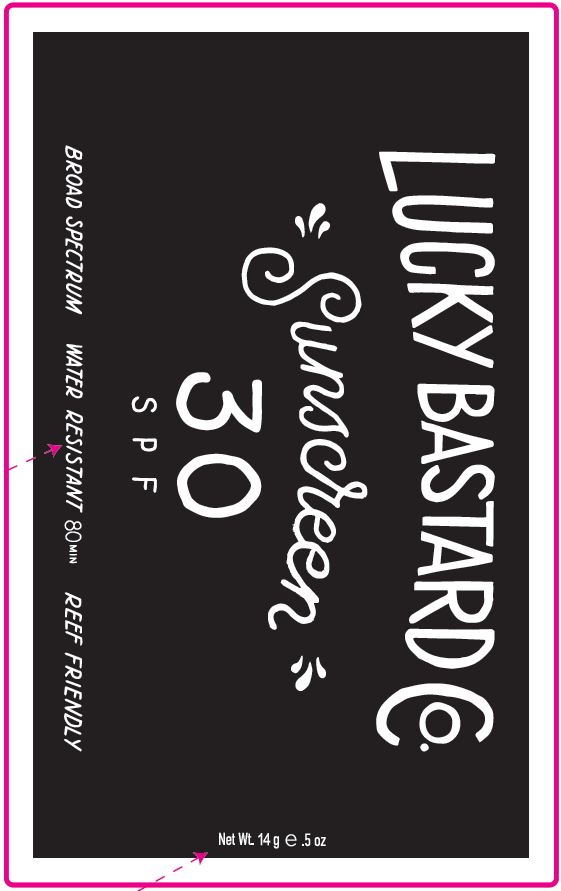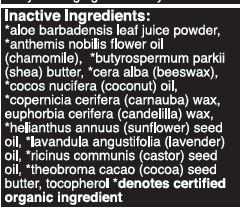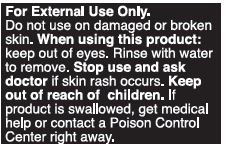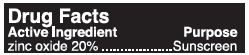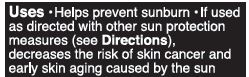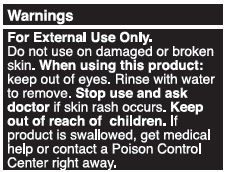 DRUG LABEL: Sunscreen
NDC: 62932-204 | Form: STICK
Manufacturer: Private Label Select Ltd CO
Category: otc | Type: HUMAN OTC DRUG LABEL
Date: 20191228

ACTIVE INGREDIENTS: ZINC OXIDE 20 g/100 g
INACTIVE INGREDIENTS: CANDELILLA WAX; SUNFLOWER OIL; SHEA BUTTER; COCOA BUTTER; CASTOR OIL; COCONUT OIL; CARNAUBA WAX; .BETA.-TOCOPHEROL; WHITE WAX; ALOE VERA LEAF

Lucky Bastard Sunscreen SPF 30